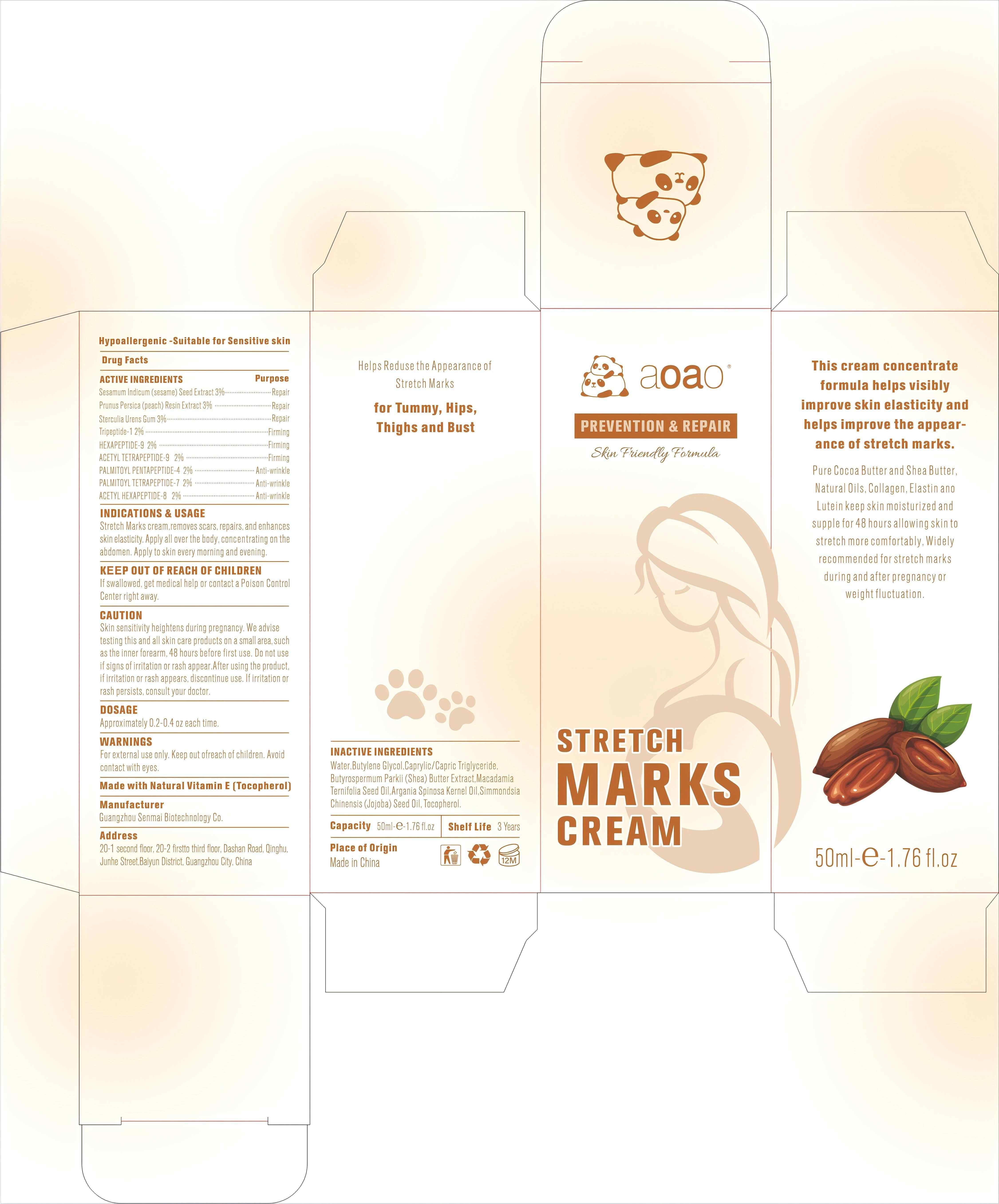 DRUG LABEL: Stretch Marks cream
NDC: 84509-006 | Form: CREAM
Manufacturer: Guangzhou Senmai Biotechnology Co.
Category: otc | Type: HUMAN OTC DRUG LABEL
Date: 20250108

ACTIVE INGREDIENTS: STERCULIA URENS WHOLE 1500 mg/50 mL; ACETYL HEXAPEPTIDE-8 1000 mg/50 mL; PREZATIDE 1000 mg/50 mL; PALMITOYL TETRAPEPTIDE-7 1000 mg/50 mL; ACETYL TETRAPEPTIDE-9 1000 mg/50 mL; SESAME SEED 1500 mg/50 mL; HEXAPEPTIDE-9 1000 mg/50 mL; PALMITOYL PENTAPEPTIDE-4 1000 mg/50 mL; PEACH 1500 mg/50 mL
INACTIVE INGREDIENTS: JOJOBA OIL; MEDIUM-CHAIN TRIGLYCERIDES; WATER; BUTYLENE GLYCOL; SHEA BUTTER; ARGAN OIL; TOCOPHEROL; MACADAMIA OIL

DESCRIPTION

Hypoallergenic -Suitable for Sensitive skin

Active Ingredients

SESAMUM INDICUM (SESAME) SEED EXTRACT 3%
PRUNUS PERSICA (PEACH) RESIN EXTRACT 3%
Sterculia Urens Gum 3%

TRIPEPTIDE-1 2%
HEXAPEPTIDE-9 2%
ACETYL TETRAPEPTIDE-9 2%
PALMITOYL PENTAPEPTIDE-4 2%

PALMITOYL TETRAPEPTIDE-7 2%
ACETYL HEXAPEPTIDE-8 2%

Purpose

Repair,Firming,Anti-wrinkle.

INDICATIONS & USAGE

Stretch Marks cream,removes scars, repairs, and enhances skin elasticity. Apply all over the body, concentrating on the abdomen. Apply to skin every morning and evening.

Keep out of reach of children

If swallowed, get medical help or contact a Poison Control Center right away

CAUTION

Skin sensitivity heightens during pregnancy. We advise testing this and all skin care products on a small area, such as the inner forearm,48 hours before first use. Do not use if signs of irritation or rash appear. After using the product, if irritation or rash appears, discontinue use. lf irritation or rash persists, consult your doctor.

DOSAGE

Approximately 0.2-0.4 oz each time.

Warnings

For external use only. Keep out ofreach of children.Avoid contact with eyes.

DESCRIPTION

Made with Natural Vitamin E (Tocopherol)

Manufacturer

Guangzhou Senmai Biotechnology Co.

Address

20-1second floor, 20-2 first to third floor,Dashan Road,Qinghu,Junhe Street, Baiyun district, Guangzhou City, China.

Capacity

50ml/1.76 Fl.oz

Inactive Ingredients

Water,Butylene Glycol,Caprylic/Capric Triglyceride,Butyrospermum Parkii (Shea) Butter Extract,Macadamia Ternifolia Seed Oil,Argania Spinosa Kernel Oil,Simmondsia Chinensis (Jojoba) Seed Oil, Tocopherol.

Shelf Life

3 Years

Place of Origin

Made in China